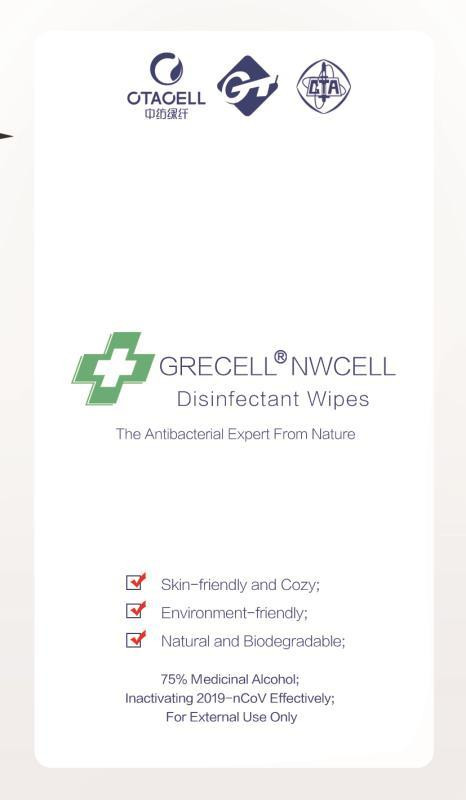 DRUG LABEL: Disinfectant Wipes
NDC: 54443-001 | Form: CLOTH
Manufacturer: China Textile Academy Green Fibre Co., Ltd
Category: otc | Type: HUMAN OTC DRUG LABEL
Date: 20200410

ACTIVE INGREDIENTS: ALCOHOL 75 mL/100 mL
INACTIVE INGREDIENTS: WATER

INACTIVE INGREDIENT

pure water and Non-woven

ACTIVE INGREDIENT

Ethanol

keep out of children

PURPOSE

Disinfection
Sterilization
No Rinseing

INDICATIONS AND USAGE

Disposable Use

DOSAGE AND ADMINISTRATION

Keep It In Below 30C Temperature; Stay Away From Fire

WARNINGS

Disposable Use;

The packing damage is for-bidden use;

Keep It In Below 30C Temperature;

Stay Away From Fire;

Do Not Mix With Chlorinated Disinfec-tants.